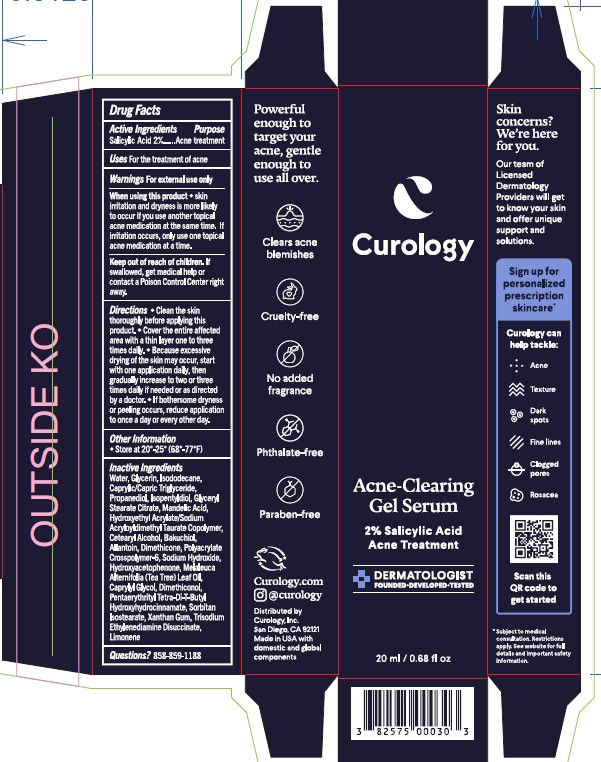 DRUG LABEL: Curology Acne-Clearing Gel Serum
NDC: 82575-500 | Form: GEL
Manufacturer: Curology, Inc.
Category: otc | Type: HUMAN OTC DRUG LABEL
Date: 20250909

ACTIVE INGREDIENTS: SALICYLIC ACID 2 g/100 mL
INACTIVE INGREDIENTS: CAPRYLYL GLYCOL; ISODODECANE; PENTAERYTHRITYL TETRA-DI-T-BUTYL HYDROXYHYDROCINNAMATE; POLYACRYLATE CROSSPOLYMER-6; ISOPENTYLDIOL; BAKUCHIOL; PROPANEDIOL; TRISODIUM ETHYLENEDIAMINE DISUCCINATE; MANDELIC ACID; DIMETHICONE; ALLANTOIN; CAPRYLIC/CAPRIC TRIGLYCERIDE; LIMONENE, (+/-)-; GLYCERIN; CETEARYL ALCOHOL; WATER; HYDROXYACETOPHENONE; MELALEUCA ALTERNIFOLIA (TEA TREE) LEAF OIL; DIMETHICONOL (100000 CST); SORBITAN ISOSTEARATE; SODIUM HYDROXIDE; XANTHAN GUM; HYDROXYETHYL ACRYLATE/SODIUM ACRYLOYLDIMETHYL TAURATE COPOLYMER (45000 MPA.S AT 1%); GLYCERYL STEARATE CITRATE

Curology Acne-Clearing Gel Serum

Drug Facts

Active Ingredients

Active Ingredient | Purpose
Salicylic Acid 2% | Acne Treatment

Uses

Uses For the treatment of acne

Warnings For external use only

When using this product

- Skin irritation and dryness is more likely to occur if you use another topical acne medication at the same time. If irritation occurs, only use one topical acne medication at a time.

KEEP OUT OF REACH OF CHILDREN

Keep out of reach of chldren. If swallowed, get midical help or contact a Poison Control Center right away.

Directions

- Clean the skin thoroughly before applying this product.
- Cover the entire affected area with a thin layer one to three times daily.
- Because excessive drying of the skin may occur, start with one application daily, then gradually increase to two or three times daily if needed or as directed by a doctor.
- If bothersome dryness or peeling occurs, reduce application to once a day or every other day.

Other Information

- Store at 20o-25o (68o-77oF)

INACTIVE INGREDIENT

Water, Glycerin, Isododecane, Caprylic/Capric Triglyceride, Propanediol, Isopentyldiol, Glyceryl Stearate Citrate, Mandelic Acid, Hydroxyethyl Acrylate/Sodium Acryloyldimethyl Taurate Copolymer, Cetearyl Alcohol, Bakuchiol, Allantoin, Dimethicone, Polyacrylate Crosspolymer-6, Sodium Hydroxide, Hydroxyacetophenone, Melaleuca Alternifolia (Tea Tree) Leaf oil, Caprylyl Glycol, Dimethiconol, Pentaerythrityl Tetra-Di-T-Butyl Hydroxyhydrocinnamate, Sorbitan Isostearate, Xanthan Gum, Trisodium Ethylenediamine Disuccinate, Limonene

Questions?

Questions? 858-859-1188

PRINCIPAL DISPLAY PANEL - 20 mL Carton

Curology

Acne-Clearing

Gel Serum

2% Salicylic Acid

Acne Treatment

Dermatologist

Founded, Developed, Tested

20 ml / 0.68 fl oz